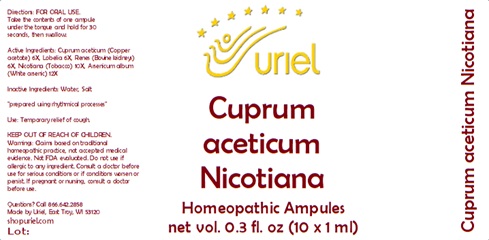 DRUG LABEL: Cuprum aceticum Nicotiana
NDC: 48951-3141 | Form: LIQUID
Manufacturer: Uriel Pharmacy Inc.
Category: homeopathic | Type: HUMAN OTC DRUG LABEL
Date: 20240116

ACTIVE INGREDIENTS: CUPRIC ACETATE 6 [hp_X]/1 mL; LOBELIA SPICATA LEAF 6 [hp_X]/1 mL; PORK KIDNEY 6 [hp_X]/1 mL; TOBACCO LEAF 10 [hp_X]/1 mL; ARSENIC TRIOXIDE 12 [hp_X]/1 mL
INACTIVE INGREDIENTS: WATER; SODIUM CHLORIDE

Cuprum aceticum Nicotiana

INDICATIONS AND USAGE

Directions: FOR ORAL USE.

DOSAGE AND ADMINISTRATION

Take the contents of one ampule under the tongue and hold for 30 seconds, then swallow.

ACTIVE INGREDIENT

Active Ingredients: Cuprum aceticum (Copper acetate) 6X, Lobelia 6X, Renes (Bovine kidneys) 6X, Nicotiana (Tobacco) 10X, Arsenicum album (White arsenic) 12X

Inactive Ingredients: Water, Salt

"prepared using rhythmical processes"

PURPOSE

Use: Temporary relief of cough.

KEEP OUT OF REACH OF CHILDREN.

WARNINGS

Warnings: Claims based on traditional homeopathic practice, not accepted medical evidence. Not FDA evaluated. Do not use if allergic to any ingredient. Consult a doctor before use for serious conditions or if conditions worsen or persist. If pregnant or nursing, consult a doctor before use.

QUESTIONS

Questions? Call 866.642.2858 Made by Uriel, East Troy, WI 53120 shopuriel.com